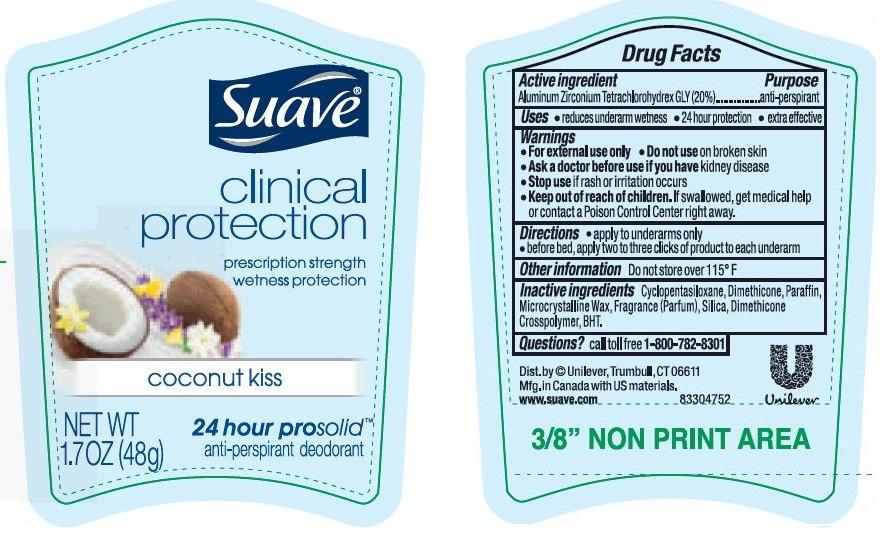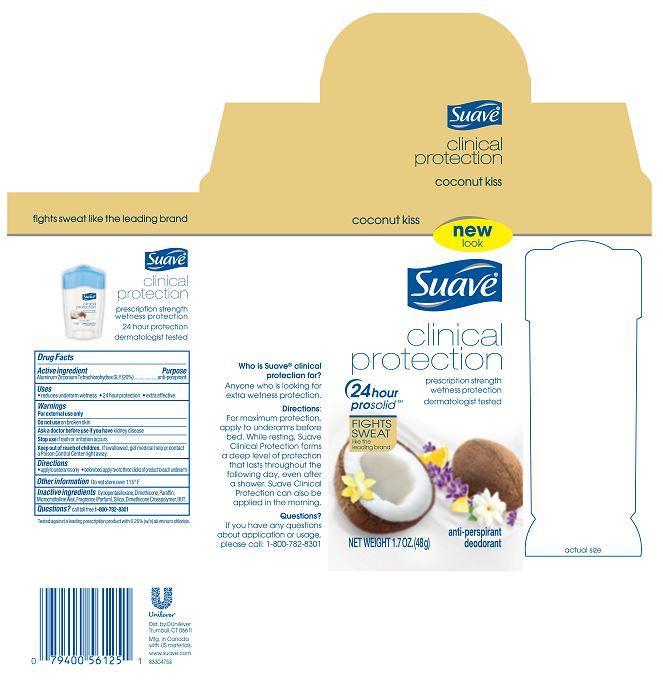 DRUG LABEL: Suave
NDC: 64942-1438 | Form: STICK
Manufacturer: Conopco Inc. d/b/a Unilever
Category: otc | Type: HUMAN OTC DRUG LABEL
Date: 20221207

ACTIVE INGREDIENTS: ALUMINUM ZIRCONIUM TETRACHLOROHYDREX GLY 20 g/100 g
INACTIVE INGREDIENTS: CYCLOMETHICONE 5; DIMETHICONE; MICROCRYSTALLINE WAX; SILICON DIOXIDE; PARAFFIN; BUTYLATED HYDROXYTOLUENE

Suave Clinical Protection Coconut Kiss antiperspirant deodorant

Active Ingredient

Aluminum Zirconium Tetrachlorohydrex GLY (20%)

Purpose
anti-perspirant

Warnings
For external use only

Do not use on broken skin

Ask a doctor before use if you have kidney disease

Stop use if rash or irritation occurs

Keep out of reach of children. If swallowed, get medical help or contact a Poison Control Center right away.

Uses
▪ reduces underarm wetness
▪ 24 hour protection
▪ extra effective

Directions
▪ apply to underarms only
▪ before bed, apply two clicks of product to each underarm

INACTIVE INGREDIENT

Inactive ingredients Cyclopentasiloxane, Dimethicone, Paraffin, Microcrystalline Wax, Fragrance (Parfum), Silica, Dimethicone Crosspolymer, BHT.

Questions? Call toll-free 1-800-782-8301